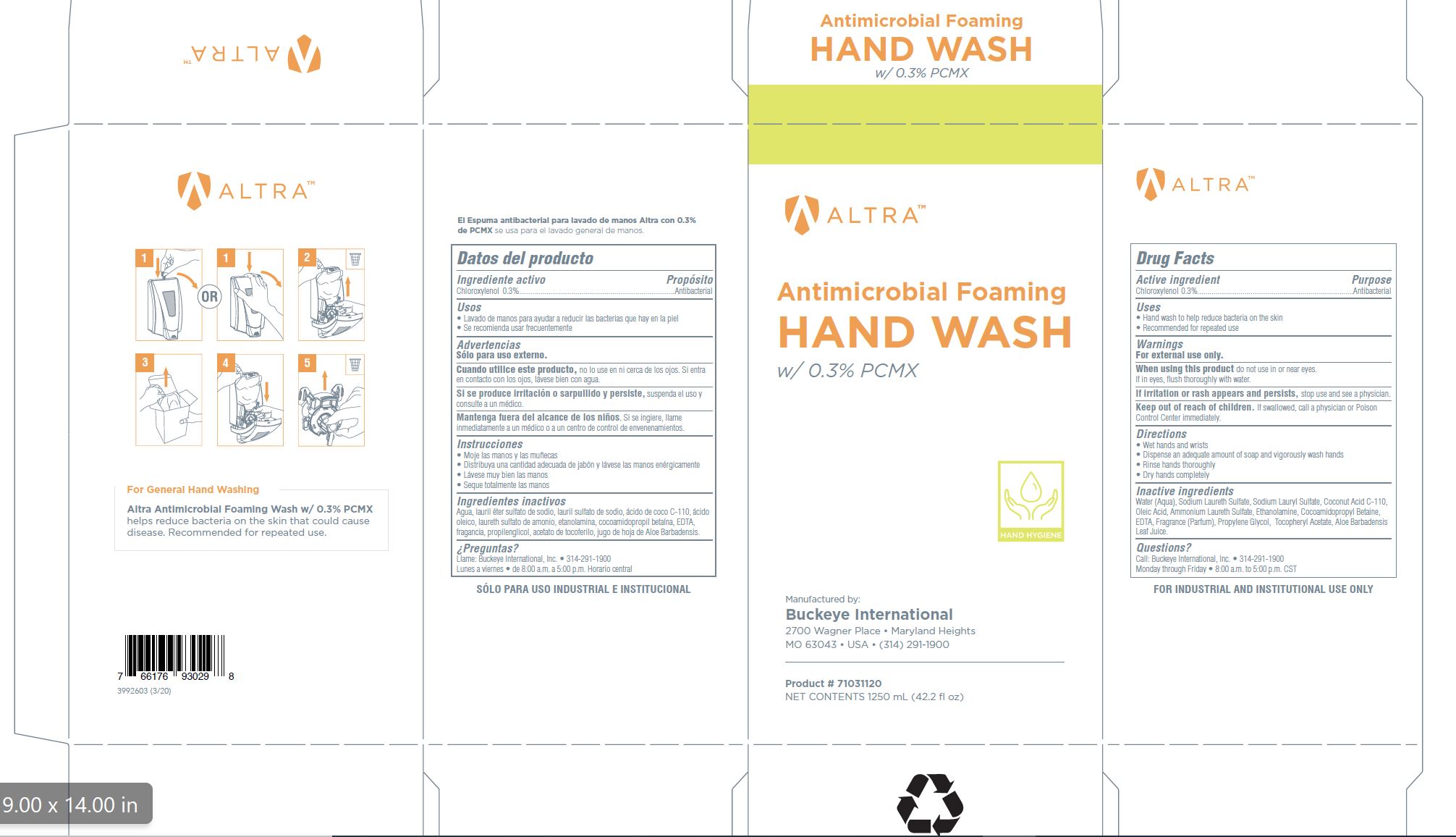 DRUG LABEL: Altra Antimicrobial Foaming Hand Wash with 0.3% PCMX
NDC: 30805-016 | Form: SOLUTION
Manufacturer: Buckeye International, Inc.
Category: otc | Type: HUMAN OTC DRUG LABEL
Date: 20250325

ACTIVE INGREDIENTS: CHLOROXYLENOL 0.3 g/100 mL
INACTIVE INGREDIENTS: COCONUT ACID; MONOETHANOLAMINE; COCAMIDOPROPYL BETAINE; EDETIC ACID; OLEIC ACID; AMMONIUM LAURETH-3 SULFATE; WATER; SODIUM LAURETH SULFATE; ALOE VERA LEAF; SODIUM LAURYL SULFATE; .ALPHA.-TOCOPHEROL ACETATE; PROPYLENE GLYCOL

Drug Facts 30805-016

Active ingredient

Chloroxylenol 0.3%

Purpose

Antibacterial

Uses

- Hand wash to help reduce bacteria on the skin
- Recommended for repeated use

Warnings

For external use only.

WHEN USING

When using this productdo not use in or near eyes.

If in eyes, flush thoroughly with water.

STOP USE

If irritation or rash appears and persists, stop use and see a physician.

Keep out of reach of children.

If swallowed, call a physician or Poison control Center immediately.

Directions

- Wet hands and wrists
- Dispense an adequate amount of soap and vigorously wash hands
- Rinse hands thoroughly
- Dry hands completely

Inactive ingredients

Water (Aqua), Sodium Laureth Sulfate, Sodium Lauryl Sulfate, Coconut Acid C-110, Oleic Acid, Ammonium Laureth Sulfate, Ethanolamine, Cocamidopropyl Betaine, EDTA, Fragrance (Parfum), Propylene Glycol, Tocopheryl Acetate, Aloe Barbadensis Leaf Juice.

Questions?

Call Buckeye International, Inc. 314-291-1900

Monday through Friday 8:00 a.m. to 5:00p.m. CST

PACKAGE LABEL

ALTRA

Antimicrobial Foaming

Hand Wash

with 0.3% PCMX

Hand Hygiene

Manufactured by:

Buckeye International

2700 Wagner Place Maryland Heights

MO 63043 USA (314) 291-1900

Product # 71031120

net Contents 1250 mL (42.2 fl oz)